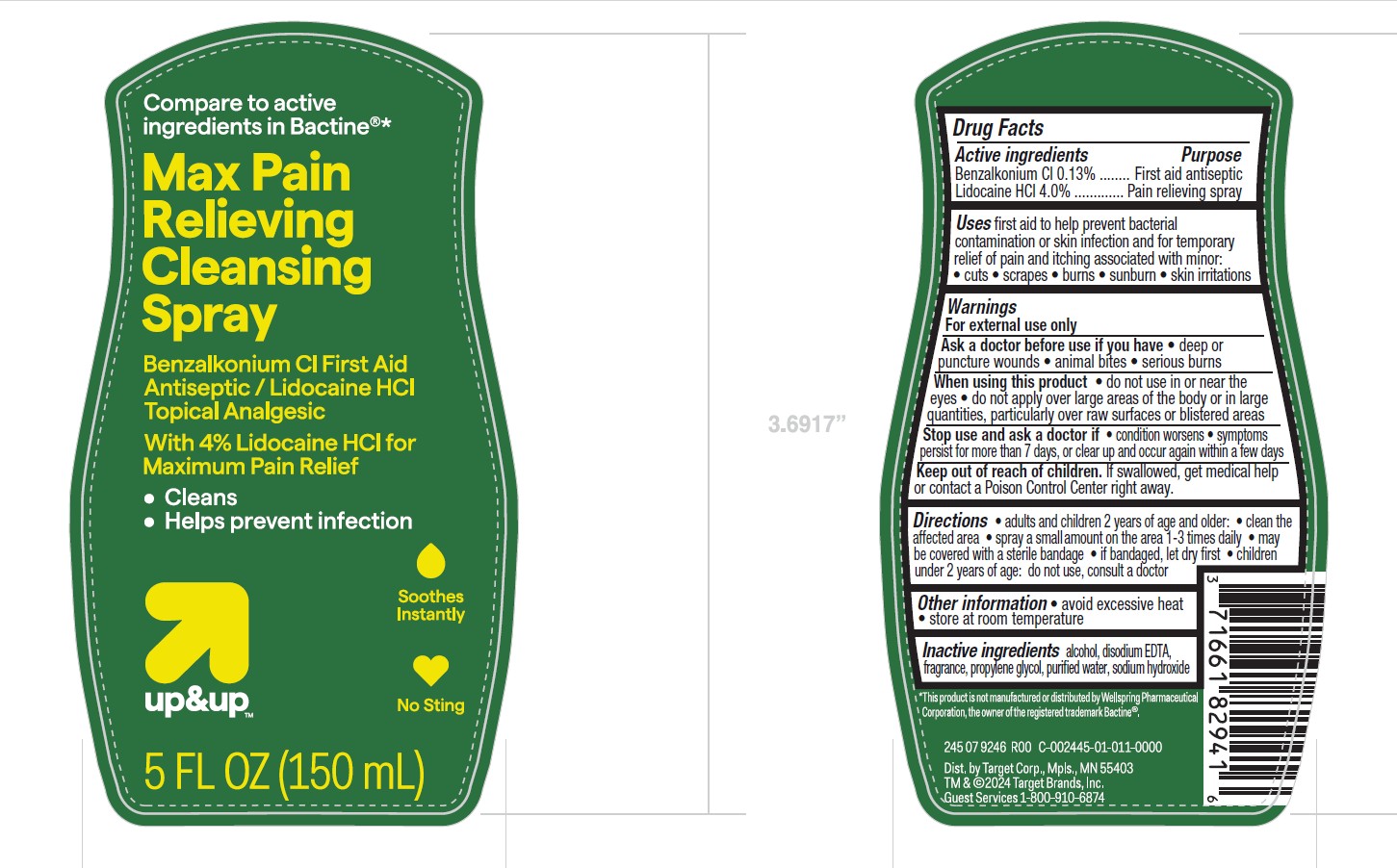 DRUG LABEL: Up and Up Max Pain Relieving Cleansing
NDC: 82442-018 | Form: LIQUID
Manufacturer: TARGET CORPORATION
Category: otc | Type: HUMAN OTC DRUG LABEL
Date: 20250121

ACTIVE INGREDIENTS: BENZALKONIUM CHLORIDE 0.13 g/100 mL; LIDOCAINE HYDROCHLORIDE 4 g/100 mL
INACTIVE INGREDIENTS: ALCOHOL; SODIUM HYDROXIDE; EDETATE DISODIUM; PROPYLENE GLYCOL; WATER

Up and Up Max Pain Relieving Cleansing Spray

Active Ingredients

Benzalkonium Cl 0.13%
Lidocaine HCl 4.0%

Purpose

First aid antiseptic
Pain relieving spray

Uses

first aid to help prevent bacterial contamination or skin infection, and for temporary relief of pain and itching associated with minor:

- cuts
- scrapes
- burns
- sunburn
- skin irritations

Warnings

For external use only

Ask a doctor before use if you have

- deep or puncture wounds
- animal bites
- serious burns

When using this product

- do not use in or near the eyes
- do not apply over large areas of the body or in large quantities, particularly over raw surfaces or blistered areas

Stop use and ask a doctor if

- condition worsens
- symptoms persist for more than 7 days, or clear up and occur again within a few days

Keep out of reach of children.

If swallowed, get medical help or contact a Poison Control Center right away.

Directions

- adults and children 2 years and older:
- clean the affected area
- spray a small amount on the area 1-3 times daily
- may be covered with a sterile bandage
- if bandaged, let dry first
- children under 2 years of age: do not use, consult a doctor

Other information

- avoid excessive heat
- store at room temperature

Inactive ingredients

alcohol, disodium EDTA, fragrances, propylene glycol, purified water, sodium hydroxide